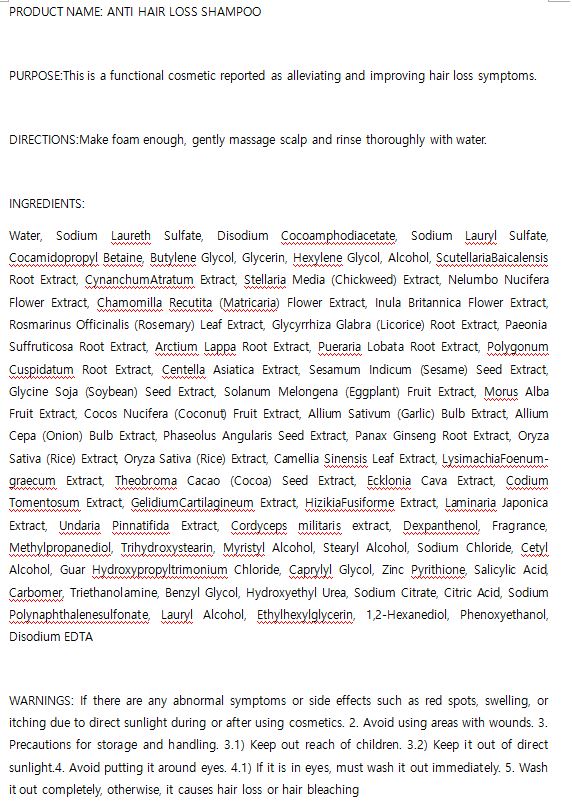 DRUG LABEL: W.SKIN ANTI HAIR LOSS
NDC: 74997-0016 | Form: SHAMPOO
Manufacturer: J&J COMPANY
Category: otc | Type: HUMAN OTC DRUG LABEL
Date: 20210507

ACTIVE INGREDIENTS: PYRITHIONE ZINC 0.312 g/100 mL; SALICYLIC ACID 0.2 g/100 mL; DEXPANTHENOL 0.5 g/100 mL
INACTIVE INGREDIENTS: GLYCERIN; WATER

J&J COMPANY

ACTIVE INGREDIENT

Zinc Pyrithione 0.312
Dexpanthenol 0.5
Salicylic acid 0.2

INACTIVE INGREDIENT

Water, Sodium Laureth Sulfate, Disodium Cocoamphodiacetate, Sodium Lauryl Sulfate, Cocamidopropyl Betaine, Butylene Glycol, Glycerin, Hexylene Glycol, Alcohol, ScutellariaBaicalensis Root Extract, CynanchumAtratum Extract, Stellaria Media (Chickweed) Extract, Nelumbo Nucifera Flower Extract, Chamomilla Recutita (Matricaria) Flower Extract, Inula Britannica Flower Extract, Rosmarinus Officinalis (Rosemary) Leaf Extract, Glycyrrhiza Glabra (Licorice) Root Extract, Paeonia Suffruticosa Root Extract, Arctium Lappa Root Extract, Pueraria Lobata Root Extract, Polygonum Cuspidatum Root Extract, Centella Asiatica Extract, Sesamum Indicum (Sesame) Seed Extract, Glycine Soja (Soybean) Seed Extract, Solanum Melongena (Eggplant) Fruit Extract, Morus Alba Fruit Extract, Cocos Nucifera (Coconut) Fruit Extract, Allium Sativum (Garlic) Bulb Extract, Allium Cepa (Onion) Bulb Extract, Phaseolus Angularis Seed Extract, Panax Ginseng Root Extract, Oryza Sativa (Rice) Extract, Oryza Sativa (Rice) Extract, Camellia Sinensis Leaf Extract, LysimachiaFoenum-graecum Extract, Theobroma Cacao (Cocoa) Seed Extract, Ecklonia Cava Extract, Codium Tomentosum Extract, GelidiumCartilagineum Extract, HizikiaFusiforme Extract, Laminaria Japonica Extract, Undaria Pinnatifida Extract, Cordyceps militaris extract, Dexpanthenol, Fragrance, Methylpropanediol, Trihydroxystearin, Myristyl Alcohol, Stearyl Alcohol, Sodium Chloride, Cetyl Alcohol, Guar Hydroxypropyltrimonium Chloride, Caprylyl Glycol, Zinc Pyrithione, Salicylic Acid, Carbomer, Triethanolamine, Benzyl Glycol, Hydroxyethyl Urea, Sodium Citrate, Citric Acid, Sodium Polynaphthalenesulfonate, Lauryl Alcohol, Ethylhexylglycerin, 1,2-Hexanediol, Phenoxyethanol, Disodium EDTA

PURPOSE

This is a functional cosmetic reported as alleviating and improving hair loss symptoms

keep out of reach of the children

INDICATIONS AND USAGE

Make foam enough, gently massage scalp and rinse thoroughly with water.

WARNINGS

If there are any abnormal symptoms or side effects such as red spots, swelling, or itching due to direct sunlight during or after using cosmetics. 2. Avoid using areas with wounds. 3. Precautions for storage and handling. 3.1) Keep out reach of children. 3.2) Keep it out of direct sunlight.

DOSAGE AND ADMINISTRATION

for external use only